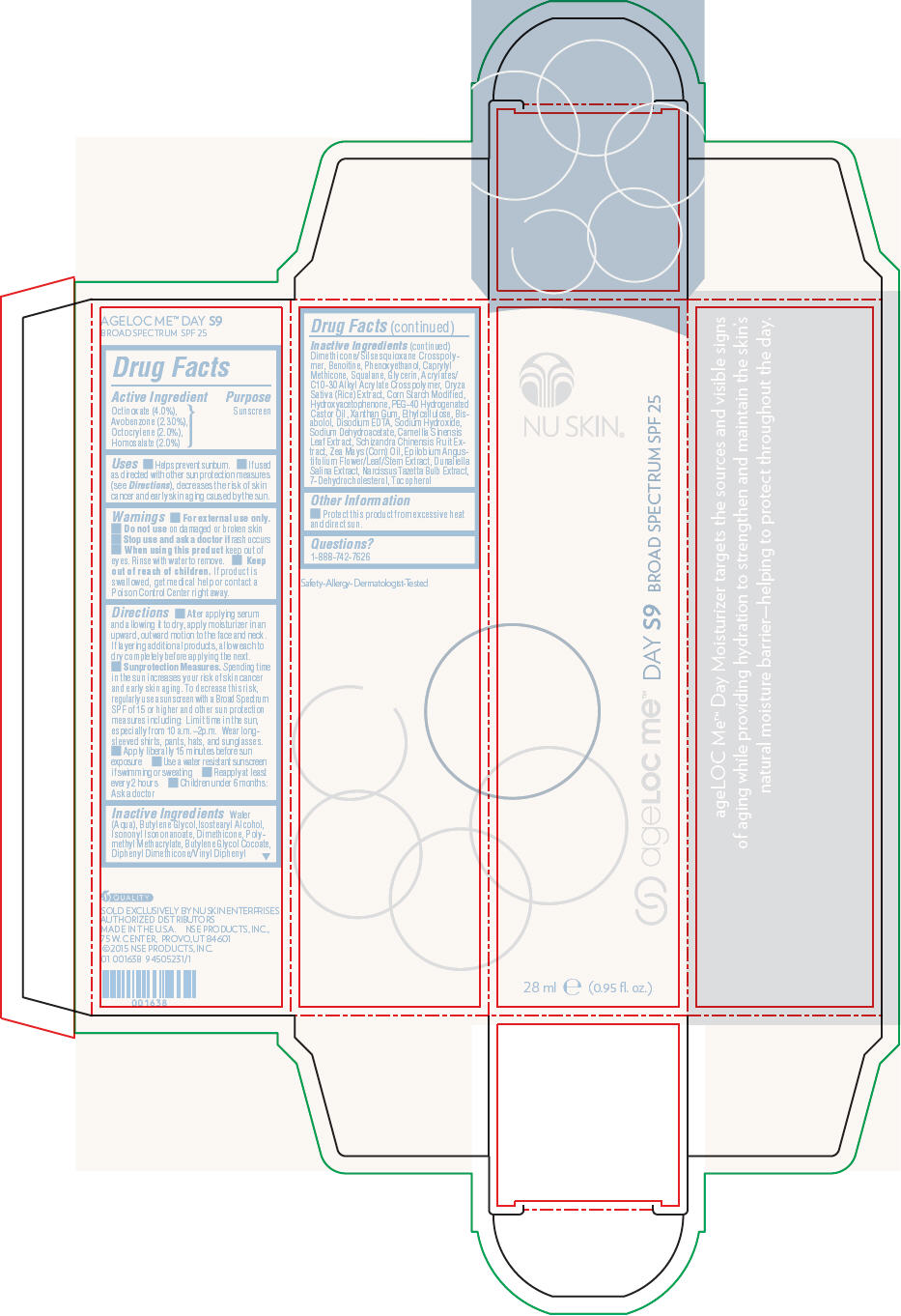 DRUG LABEL: Nu Skin ageLOC Me Day S9 Broad Spectrum SPF 25
NDC: 62839-1638 | Form: LOTION
Manufacturer: NSE Products, Inc.
Category: otc | Type: HUMAN OTC DRUG LABEL
Date: 20241230

ACTIVE INGREDIENTS: Octinoxate 40 mg/1 mL; Avobenzone 23 mg/1 mL; Octocrylene 20 mg/1 mL; Homosalate 20 mg/1 mL
INACTIVE INGREDIENTS: Water; Butylene Glycol; Isostearyl Alcohol; Isononyl Isononanoate; Dimethicone; Phenoxyethanol; Caprylyl Trisiloxane; Squalane; Glycerin; Rice Germ; Polyoxyl 40 Hydrogenated Castor Oil; Xanthan Gum; ETHYLCELLULOSE, UNSPECIFIED; Levomenol; Edetate Disodium; Sodium Hydroxide; Sodium Dehydroacetate; Green Tea Leaf; Schisandra Chinensis Fruit; Corn Oil; Epilobium Angustifolium Flowering Top; Dunaliella Salina; Narcissus Tazetta Bulb; 7-Dehydrocholesterol; Tocopherol

Nu Skin® ageLOC Me™ Day S9 Broad Spectrum SPF 25

Drug Facts

Active Ingredient

Octinoxate (4.0%),
Avobenzone (2.30%),
Octocrylene (2.0%),
Homosalate (2.0%)

Purpose

Sunscreen

Uses

- Helps prevent sunburn.
- If used as directed with other sun protection measures (see Directions), decreases the risk of skin cancer and early skin aging caused by the sun.

Warnings

- For external use only.

- Do not use on damaged or broken skin

- Stop use and ask a doctor if rash occurs

- When using this product keep out of eyes. Rinse with water to remove.

- Keep out of reach of children. If product is swallowed, get medical help or contact a Poison Control Center right away.

Directions

- After applying serum and allowing it to dry, apply moisturizer in an upward, outward motion to the face and neck. If layering additional products, allow each to dry completely before applying the next.
- Sunprotection Measures. Spending time in the sun increases your risk of skin cancer and early skin aging. To decrease this risk, regularly use a sunscreen with a Broad Spectrum SPF of 15 or higher and other sun protection measures including: Limit time in the sun, especially from 10 a.m.–2p.m. Wear long-sleeved shirts, pants, hats, and sunglasses.
- Apply liberally 15 minutes before sun exposure
- Use a water resistant sunscreen if swimming or sweating
- Reapply at least every 2 hours
- Children under 6 months: Ask a doctor

Inactive Ingredients

Water (Aqua), Butylene Glycol,Isostearyl Alcohol, Isononyl Isononanoate, Dimethicone, Polymethyl Methacrylate, Butylene Glycol Cocoate, Diphenyl Dimethicone/Vinyl Diphenyl Dimethicone/Silsesquioxane Crosspolymer, Benoitine, Phenoxyethanol, Caprylyl Methicone, Squalane, Glycerin, Acrylates/C10-30 Alkyl Acrylate Crosspolymer, Oryza Sativa (Rice) Extract, Corn Starch Modified, Hydroxyacetophenone, PEG-40 Hydrogenated Castor Oil, Xanthan Gum, Ethylcellulose, Bisabolol, Disodium EDTA, Sodium Hydroxide, Sodium Dehydroacetate, Camellia Sinensis Leaf Extract, Schizandra Chinensis Fruit Extract, Zea Mays (Corn) Oil, Epilobium Angustifolium Flower/Leaf/Stem Extract, Dunaliella Salina Extract, Narcissus Tazetta Bulb Extract, 7-Dehydrocholesterol, Tocopherol

Other Information

- Protect this product from excessive heat and direct sun.

Questions?

1-888-742-7626

PRINCIPAL DISPLAY PANEL - 28 ml Cartridge Carton

NU SKIN®

ageLOC me™ DAY S9 BROAD SPECTRUM SPF 25

28 ml e (0.95 fl. oz.)